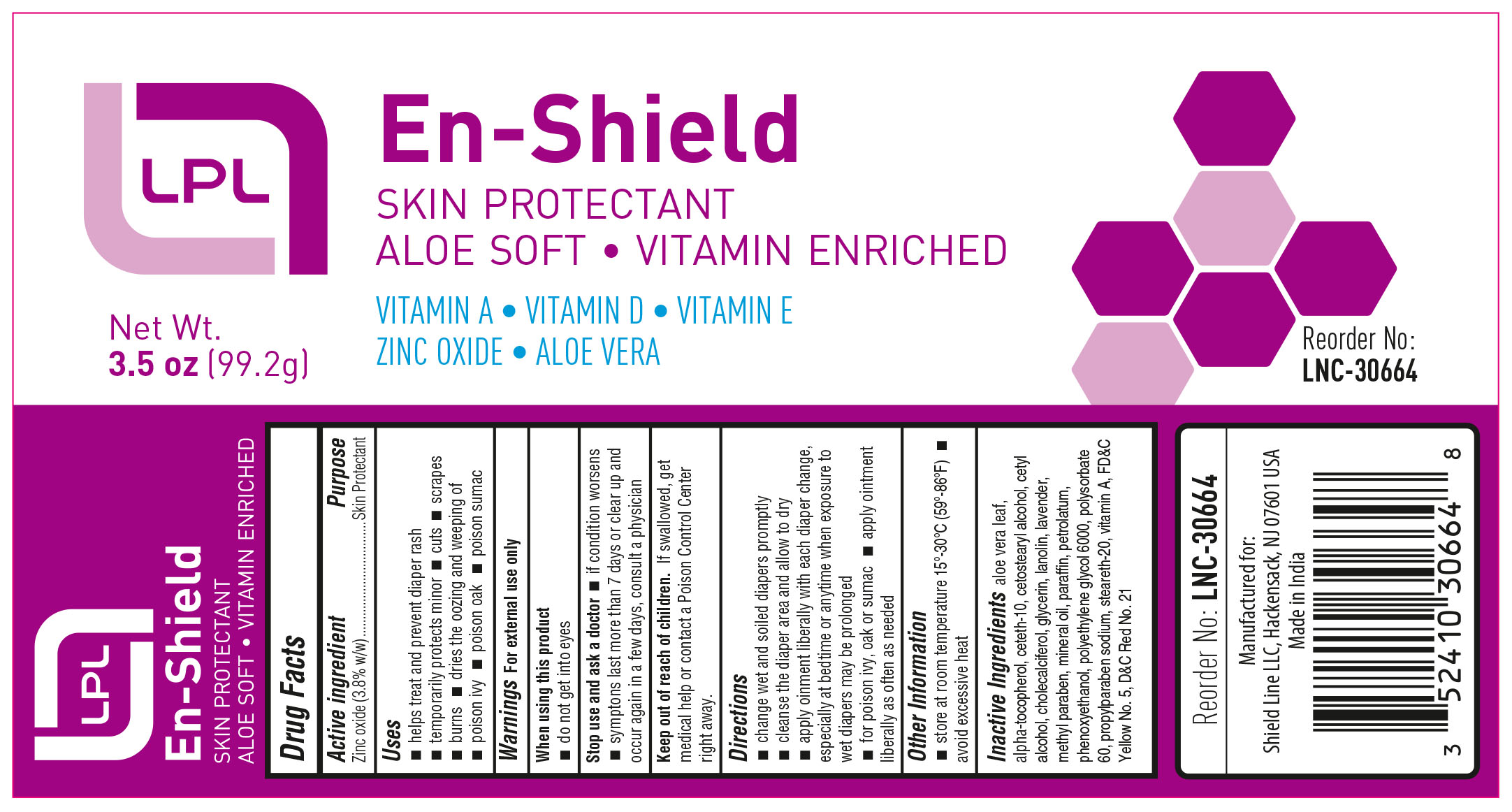 DRUG LABEL: Lincoln
NDC: 69636-3066 | Form: CREAM
Manufacturer: Lincoln Pharmaceuticals Ltd.
Category: otc | Type: HUMAN OTC DRUG LABEL
Date: 20170110

ACTIVE INGREDIENTS: ZINC OXIDE 3.8 g/100 g
INACTIVE INGREDIENTS: CETYL ALCOHOL; CETOSTEARYL ALCOHOL; ALOE VERA LEAF; .ALPHA.-TOCOPHEROL; LANOLIN; PROPYLPARABEN SODIUM; STEARETH-20; CETETH-10; PETROLATUM; POLYETHYLENE GLYCOL 6000; POLYSORBATE 60; TROLAMINE; VITAMIN A; WATER; D&C RED NO. 21; GLYCERIN; LAVENDER OIL; METHYLPARABEN; MINERAL OIL; PARAFFIN; CHOLECALCIFEROL; PHENOXYETHANOL; FD&C YELLOW NO. 5

ACTIVE INGREDIENT

Zinc Oxide (3.8% w/w)

PURPOSE

Skin Protectant

USES

- helps treat and prevent diaper rash
- temporarily protects minor cuts, scrapes, burns
- dries the oozing and weeping of poison ivy, poison oak, poison sumac

WARNINGS

FOR EXTERNAL USE ONLY

When using this product

- Do not get into the eyes

Stop use and ask a doctor

- If condition worsens
- symptoms last more than 7 days or clear up and occur again in a few days, consult a physician

Keep out of reach of children

- if swallowed, get medical help or contact the Poison Control Center right away

DIRECTIONS

- change wet and soiled diapers promptly
- cleanse the diaper area and allow to dry
- apply ointment liberally with each diaper change, especially at bedtime or anytime when exposure to wet diapers may be prolonged
- for poison ivy, oak, and sumac
- apply ointment liberally as needed

OTHER INFORMATION

- store at room temperature 15°C-30°C (59-86 F)
- avoid excessive heat

INACTIVE INGREDIENTS

aloe vera leaf, alpha-tocopherol, ceteth-10, cetostearyl alcohol, cetyl alcohol, cholecalciferol, glycerin, lanolin, lavender, methyl paraben, mineral oil, paraffin, petrolatum, phenoxyethanol, polyethylene glycol 6000, polysorbate 60, propylparaben sodium, steareth-20, trolamine, vitamin A, water, FD&C Yellow No. 5, D&C Red No. 21